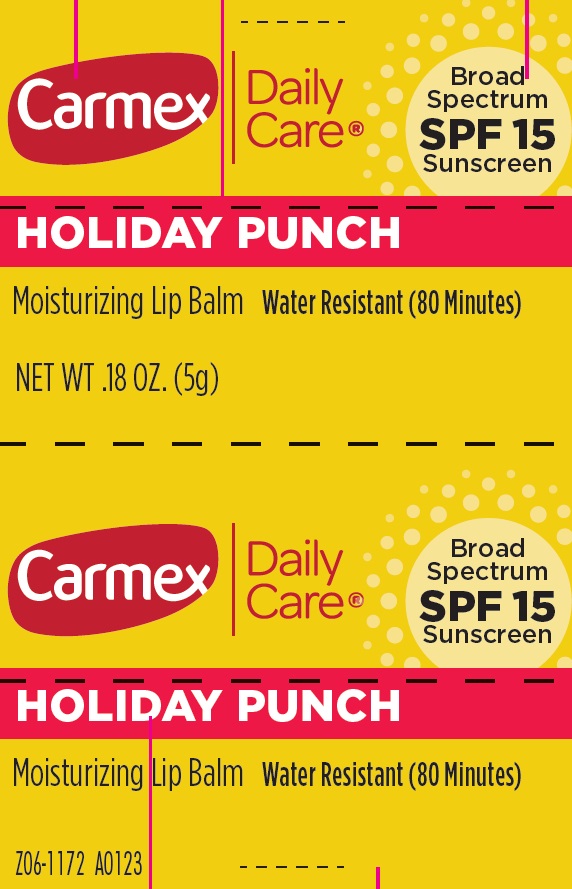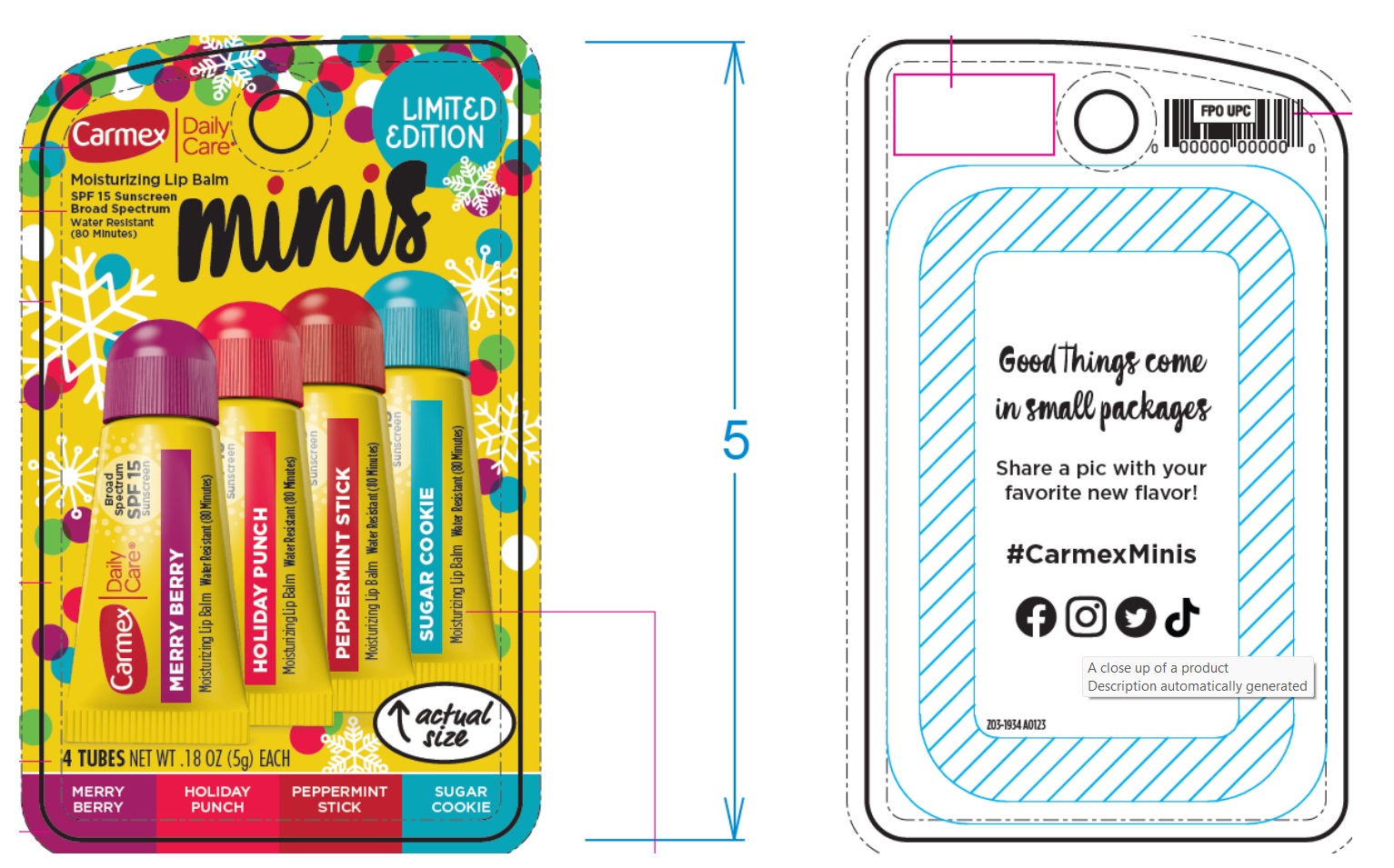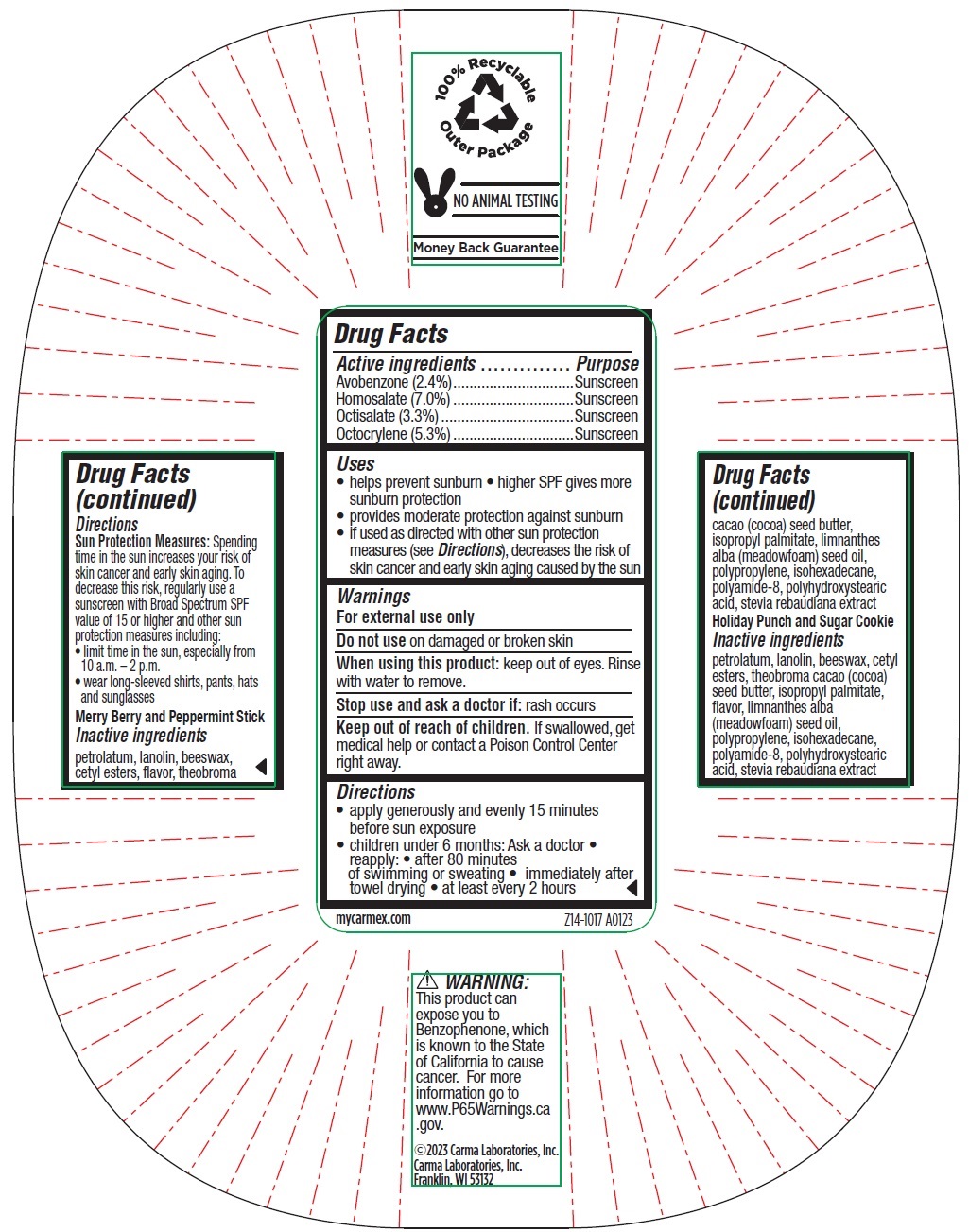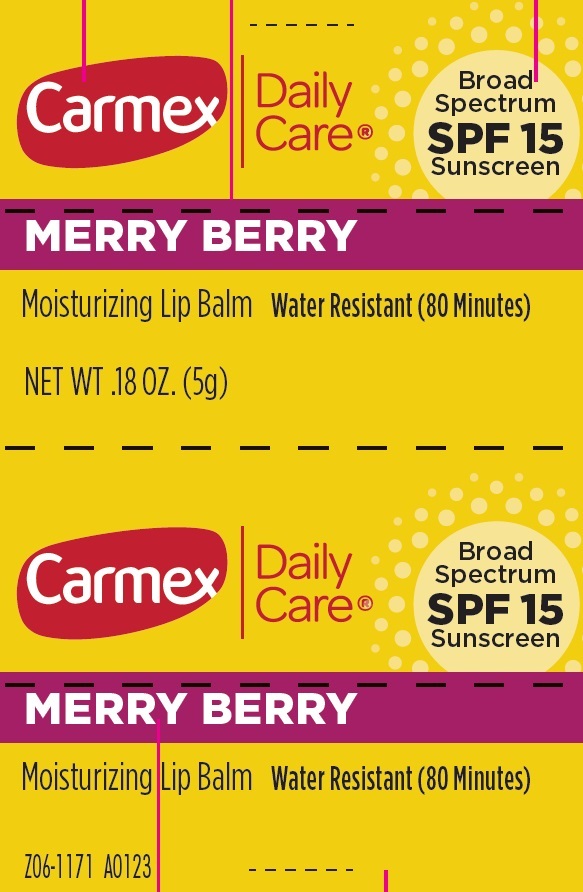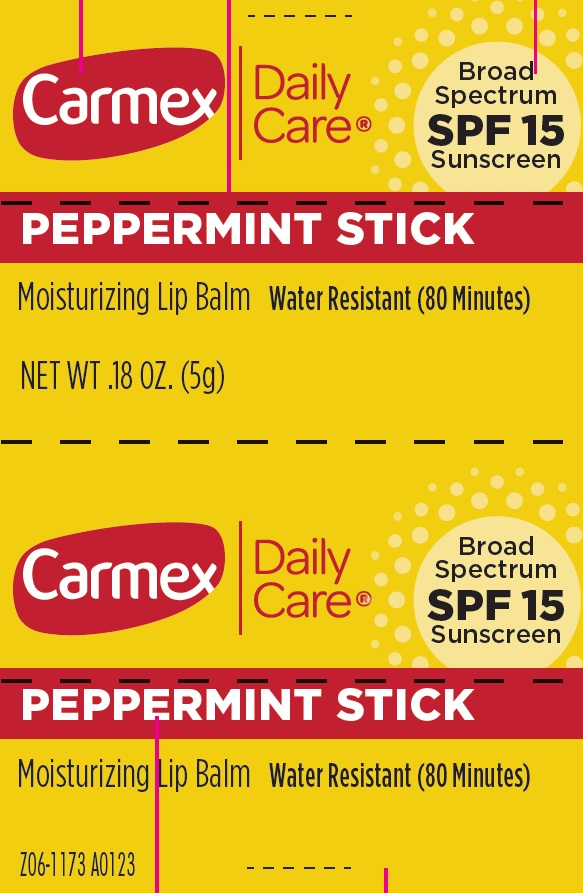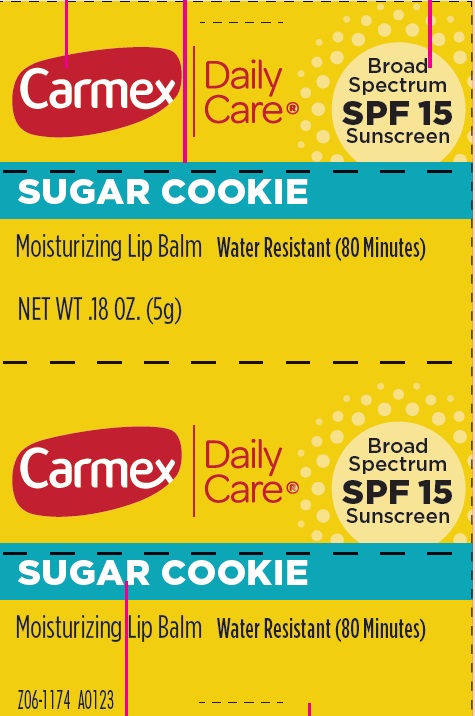 DRUG LABEL: Carmex Daily Care Moisturizing Lip Balm SPF15 Broad Sprectrum Minis Holiday
NDC: 10210-0073 | Form: KIT | Route: TOPICAL
Manufacturer: Carma Laboratories, Inc.
Category: otc | Type: HUMAN OTC DRUG LABEL
Date: 20240402

ACTIVE INGREDIENTS: AVOBENZONE 24 mg/1 g; HOMOSALATE 70 mg/1 g; OCTISALATE 33 mg/1 g; OCTOCRYLENE 53 mg/1 g; AVOBENZONE 24 mg/1 g; HOMOSALATE 70 mg/1 g; OCTISALATE 33 mg/1 g; OCTOCRYLENE 53 mg/1 g; AVOBENZONE 24 mg/1 g; HOMOSALATE 70 mg/1 g; OCTISALATE 33 mg/1 g; OCTOCRYLENE 53 mg/1 g; AVOBENZONE 24 mg/1 g; HOMOSALATE 70 mg/1 g; OCTISALATE 33 mg/1 g; OCTOCRYLENE 53 mg/1 g
INACTIVE INGREDIENTS: PETROLATUM; LANOLIN; YELLOW WAX; CETYL ESTERS WAX; COCOA BUTTER; ISOPROPYL PALMITATE; MEADOWFOAM SEED OIL; ISOHEXADECANE; PETROLATUM; LANOLIN; YELLOW WAX; CETYL ESTERS WAX; COCOA BUTTER; ISOPROPYL PALMITATE; MEADOWFOAM SEED OIL; ISOHEXADECANE; PETROLATUM; LANOLIN; YELLOW WAX; CETYL ESTERS WAX; COCOA BUTTER; ISOPROPYL PALMITATE; MEADOWFOAM SEED OIL; ISOHEXADECANE; PETROLATUM; LANOLIN; YELLOW WAX; CETYL ESTERS WAX; COCOA BUTTER; ISOPROPYL PALMITATE; MEADOWFOAM SEED OIL; ISOHEXADECANE

Carmex Daily Care Moisturizing Lip Balm SPF15 Broad Sprectrum Minis Holiday, Kit

Active ingredients

Avobenzone (2.4%)

Homosalate (7.0%)

Octisalate (3.3%)

Octocrylene (5.3%)

Purpose

Sunscreen

Uses

- helps prevent sunburn
- higher SPF gives more sunburn protection
- provides moderate protection against sunburn
- if used as directed with other sun protection measures (see Directions), decreases the risk of skin cancer and early skin aging caused by the sun

Warnings

For external use only

Do not use

on damaged or broken skin

When using this product:

keep out of eyes. Rinse with water to remove.

Stop use and ask a doctor if:

rash occurs

Keep out of reach of children.

If swallowed, get medical help or contact a Posion Control Center right away.

Directions

• apply generously and evenly 15 minutes before sun exposure
• children under 6 months: Ask a doctor • reapply: • after 80 minutes of swimming or sweating • immediately after towel drying • at least every 2 hours

Sun Protection Measures:Spending time in the sun increases your risk of skin cancer and early skin aging. To decrease this risk, regularly use a sunscreen with Broad Spectrum SPF value of 15 or higher and other sun protection measures including:
• limit time in the sun, especially from 10 a.m. – 2 p.m.
• wear long-sleeved shirts, pants, hats and sunglasses

Inactve ingredients

Merry Berry and Peppermint Stick
petrolatum, lanolin, beeswax, cetyl esters, flavor, theobroma cacao (cocoa) seed butter, isopropyl palmitate, limnanthes alba (meadowfoam) seed oil, polypropylene, isohexadecane, polyamide-8, polyhydroxystearic acid, stevia rebaudiana extract

Holiday Punch and Sugar Cookie
petrolatum, lanolin, beeswax, cetyl esters, theobroma cacao (cocoa) seed butter, isopropyl palmitate, flavor, limnanthes alba (meadowfoam) seed oil, polypropylene, isohexadecane, polyamide-8, polyhydroxystearic acid, stevia rebaudiana extract